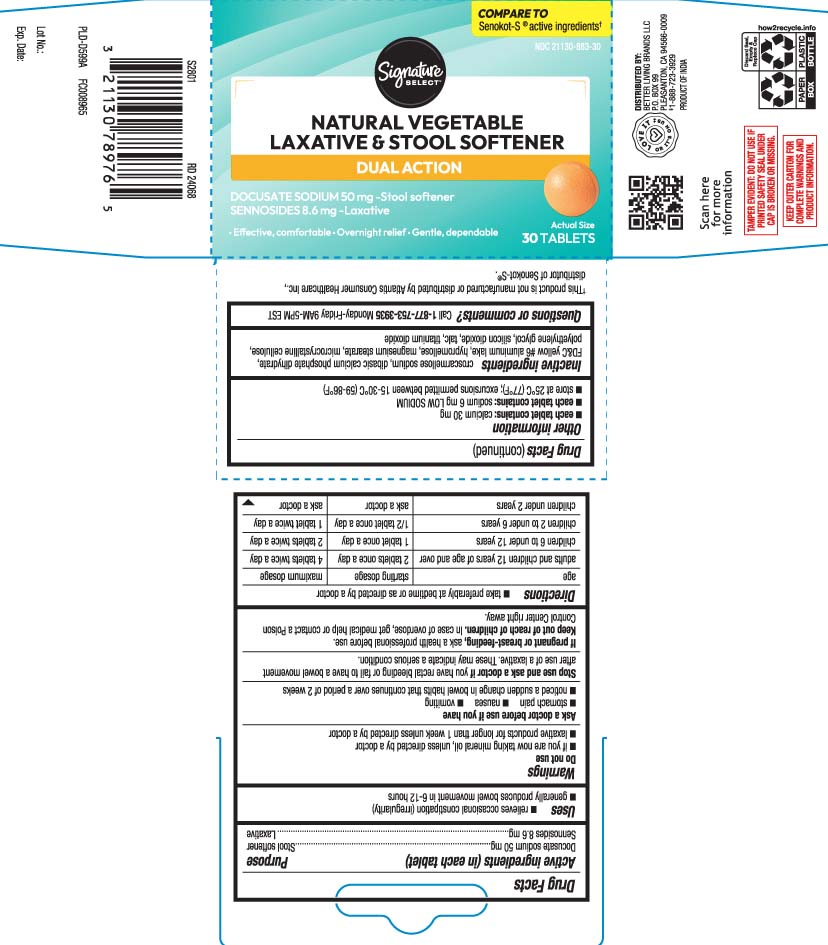 DRUG LABEL: Senna S
NDC: 21130-883 | Form: TABLET
Manufacturer: Safeway, Inc.
Category: otc | Type: HUMAN OTC DRUG LABEL
Date: 20260105

ACTIVE INGREDIENTS: DOCUSATE SODIUM 50 mg/1 1; SENNOSIDES 8.6 mg/1 1
INACTIVE INGREDIENTS: CROSCARMELLOSE SODIUM; DIBASIC CALCIUM PHOSPHATE DIHYDRATE; FD&C YELLOW NO. 6; HYPROMELLOSES; MAGNESIUM STEARATE; CELLULOSE, MICROCRYSTALLINE; POLYETHYLENE GLYCOL, UNSPECIFIED; SILICON DIOXIDE; TALC; TITANIUM DIOXIDE; ALUMINUM OXIDE

Drug Facts

Active ingredients (in each tablet)

Docusate sodium 50 mg
Sennosides 8.6 mg

Purpose

Stool softener

Laxative

Uses

- relieves occasional constipation (irregularity)
- generally produces bowel movement in 6-12 hours

Warnings

Do not use

- if you are now taking mineral oil, unless directed by a doctor
- laxative products for longer than 1 week unless directed by a doctor

Ask a doctor before use if you have

- stomach pain
- nausea
- vomiting
- noticed a sudden change in bowel habits that continues over a period of 2 weeks

Stop use and ask a doctor if

you have rectal bleeding or fail to have a bowel movement after use of a laxative. These may indicate a serious condition.

If pregnant or breast-feeding,

ask a health professional before use.

Keep out of reach of children.

In case of overdose, get medical help or contact a Poison Control Center right away.

Directions

- take preferably at bedtime or as directed by a doctor

age | starting dosage | maximum dosage
adults and children 12 years of age and over | 2 tablets once a day | 4 tablets twice a day
children 6 to under 12 years | 1 tablet once a day | 2 tablets twice a day
children 2 to under 6 years | 1/2 tablet once a day | 1 tablet twice a day
children under 2 years | ask a doctor | ask a doctor

Other information

- each tablet contains: calcium 30 mg
- each tablet contains: sodium 6 mg LOW SODIUM
- store at 25ºC (77ºF); excursions permitted between 15-30ºC (59-86ºF)

Inactive ingredients

croscarmellose sodium, dibasic calcium phosphate dihydrate, FD&C yellow #6 aluminum lake, hypromellose, magnesium stearate, microcrystalline cellulose, polyethylene glycol, silicon dioxide, talc, titanium dioxide

Questions or comments?

Call 1-877-753-3935 Monday-Friday 9AM-5PM EST

Principal Display Panel

COMPARE TO Senokot-S® active ingredients†

NATURAL VEGETABLE

LAXATIVE & STOOL SOFTENER

DUAL ACTION

DOCUSATE SODIUM 50 mg-Stool softener

SENNOSIDES 8.6 mg-Laxative

- Effective, comfortable
- Overnight Relief
- Gentle, Dependable

TABLETS

†This product is not manufactured or distributed by Atlantis Consumer Healthcare Inc., distributor of Senokot-S®.

TAMPER EVIDENT: DO NOT USE IF PRINTED SAFETY SEAL UNDER CAP IS BROKEN OR MISSING.

KEEP OUTER CARTON FOR COMPLETE WARNINGS AND PRODUCT INFORMATION.

DISTRIBUTED BY

BETTER LIVING BRANDS LLC

P.O. BOX 99, PLEASANTON, CA 94566-0009

Product Labeling

SIGNATURE SELECT Laxative & Stool Softener